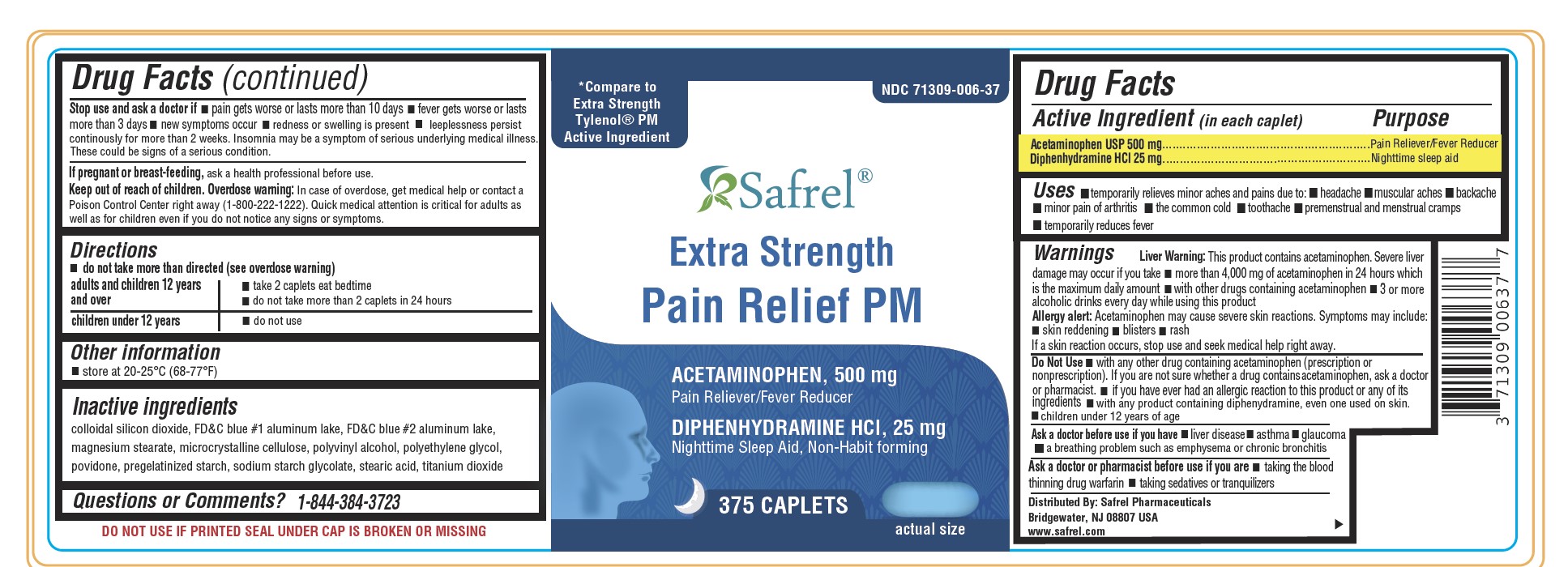 DRUG LABEL: EXTRA STRENGTH NO-PAIN PM
NDC: 71309-006 | Form: TABLET
Manufacturer: Safrel Pharmaceuticals, LLC.
Category: otc | Type: HUMAN OTC DRUG LABEL
Date: 20210531

ACTIVE INGREDIENTS: ACETAMINOPHEN 500 mg/1 1; DIPHENHYDRAMINE HYDROCHLORIDE 25 mg/1 1
INACTIVE INGREDIENTS: FD&C BLUE NO. 1; FD&C BLUE NO. 2; HYPROMELLOSES; MAGNESIUM STEARATE; POLYETHYLENE GLYCOL, UNSPECIFIED; CELLULOSE, MICROCRYSTALLINE; STARCH, PREGELATINIZED CORN; PROPYLENE GLYCOL; STEARIC ACID; TITANIUM DIOXIDE

Pain Relief PM - Acetaminophen and Diphenhydramine HCl

Drug Facts

ACTIVE INGREDIENT

Active ingredients (in each caplet) | Purpose
Acetaminophen 500 mg | Pain reliever
Diphenhydramine HCl 25 mg | Nighttime sleep aid

Uses

temporary relief of occasional headaches and minor aches and pains with accompanying sleeplessness

Warnings

Liver warning

This product contains acetaminophen. Severe liver damage may occur if you take

- more than 4,000 mg of acetaminophen in 24 hours
- with other drugs containing acetaminophen
- 3 or more alcoholic drinks every day while using this product

Do not use

- with any other drug containing acetaminophen (prescription or nonprescription). If you are not sure whether a drug contains acetaminophen, ask a doctor or pharmacist.
- with any product containing diphenhydramine, even one used on skin
- in children under 12 years of age
- if you have ever had an allergic reaction to this product or any of its ingredients

Ask a doctor before use if you have

- liver disease
- a breathing problem such as emphysema or chronic bronchitis
- trouble urinating due to an enlarged prostate gland
- glaucoma

Ask a doctor or pharmacist before use if you are

- taking the blood thinning drug warfarin
- taking sedatives or tranquilizers

When using this product

- drowsiness will occur
- avoid alcoholic drinks
- do not drive a motor vehicle or operate machinery

Stop use and ask a doctor if

- sleeplessness persists continuously for more than 2 weeks. Insomnia may be a symptom of serious underlying medical illness.
- pain gets worse or lasts more than 10 days
- fever gets worse or lasts more than 3 days
- redness or swelling is present
- new symptoms occur

These could be signs of a serious condition.

PREGNANCY OR BREAST FEEDING

If pregnant or breast-feeding, ask a health professional before use.

Keep out of reach of children.

Overdose warning

Taking more than the recommended dose (overdose) may cause liver damage. In case of overdose, get medical help or contact a Poison Control Center right away. (1-800-222-1222) Quick medical attention is critical for adults as well as for children even if you do not notice any signs or symptoms.

Directions

- do not take more than directed (see overdose warning)
- adults and children 12 years and over: take 2 caplets at bedtime
- do not take more than 2 caplets of this product in 24 hours
- children under 12 years: do not use this adult product in children under 12 years of age; this will provide more than the recommended dose (overdose) and may cause liver damage

Other information

- store between 20-25°C (68-77°F)
- do not use if pouch is torn or open
- see side panel for lot number and expiration date

Inactive ingredients

colloidal silicon dioxide, FD&C blue #1 aluminum lake, FD&C blue #2 aluminum lake,
magnesium stearate, microcrystalline cellulose, polyvinyl alcohol, polyethylene glycol,
povidone, pregelatinized starch, sodium starch glycolate, stearic acid, titanium dioxide

Questions or comments?

1-844-384-3723 (Mon-Fri 9am-5pm EST) or www.safrelpharma.com

PRINCIPAL DISPLAY PANEL

Compare to the Active Ingredients in
Tylenol PM ®*

Pain Relief PM

★Pain Reliever ★Nighttime Sleep Aid

Acetaminophen, Diphenhydramine HCl